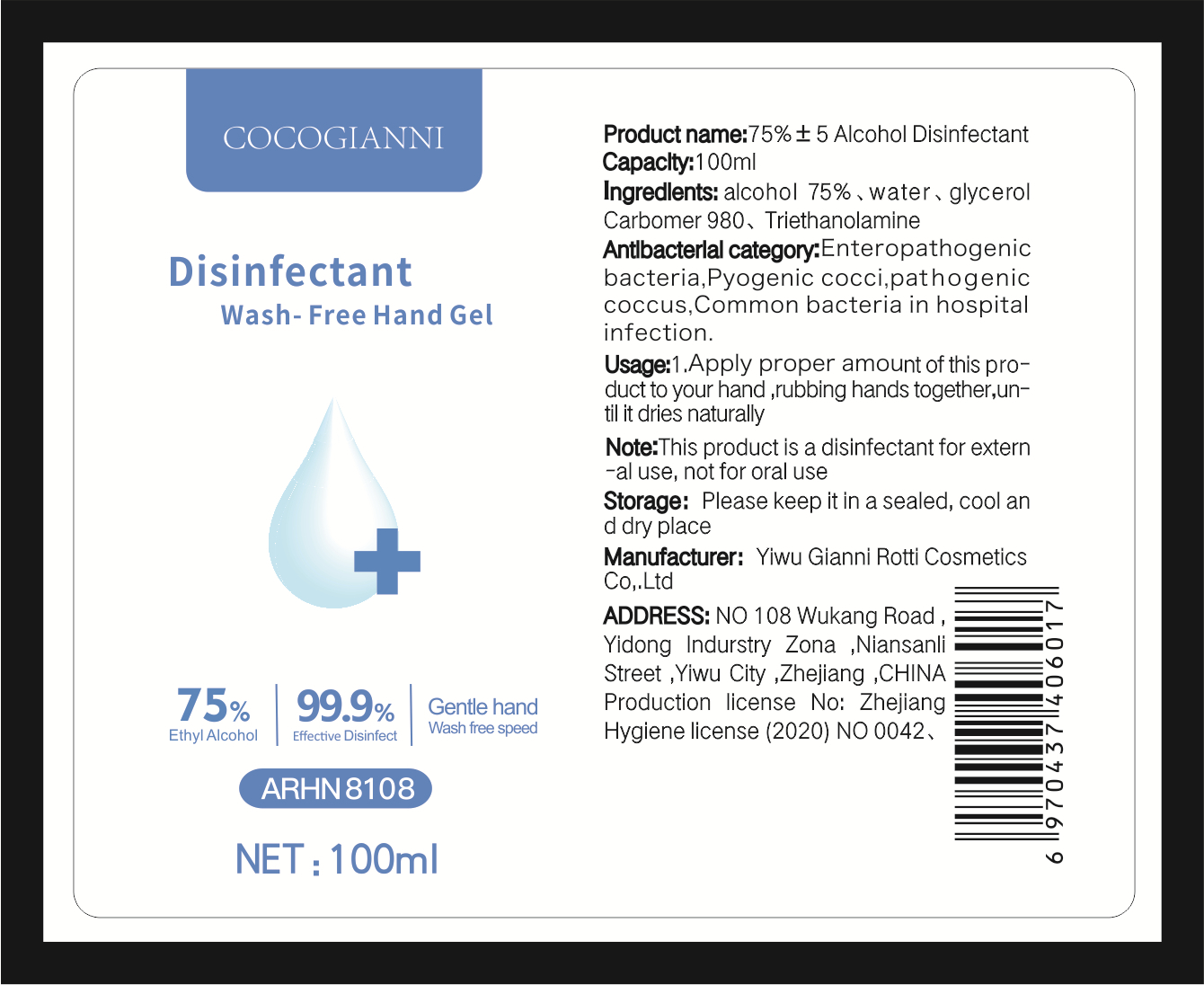 DRUG LABEL: disinfectant wash free hand gel
NDC: 54282-002 | Form: GEL
Manufacturer: YIWU GIANNI ROTTI COSMETICS CO., LTD.
Category: otc | Type: HUMAN OTC DRUG LABEL
Date: 20200410

ACTIVE INGREDIENTS: ALCOHOL 75 mL/100 mL
INACTIVE INGREDIENTS: GLYCERIN; WATER; CARBOMER 980; TROLAMINE

keep out of reach of children

ACTIVE INGREDIENT

Alcohol CAS 64-17-5

INDICATIONS AND USAGE

Apply proper amount of this product to your hand ,rubbing hands together,until it dries naturally

WARNINGS

This product is a disinfectant for external use, not for oral use

DOSAGE AND ADMINISTRATION

Please keep it in a sealed, cool and dry place

INACTIVE INGREDIENT

glycerol ,Carbomer980, Triethanolamine,Water

PURPOSE

Disinfection
Sterilization
No Rinseing